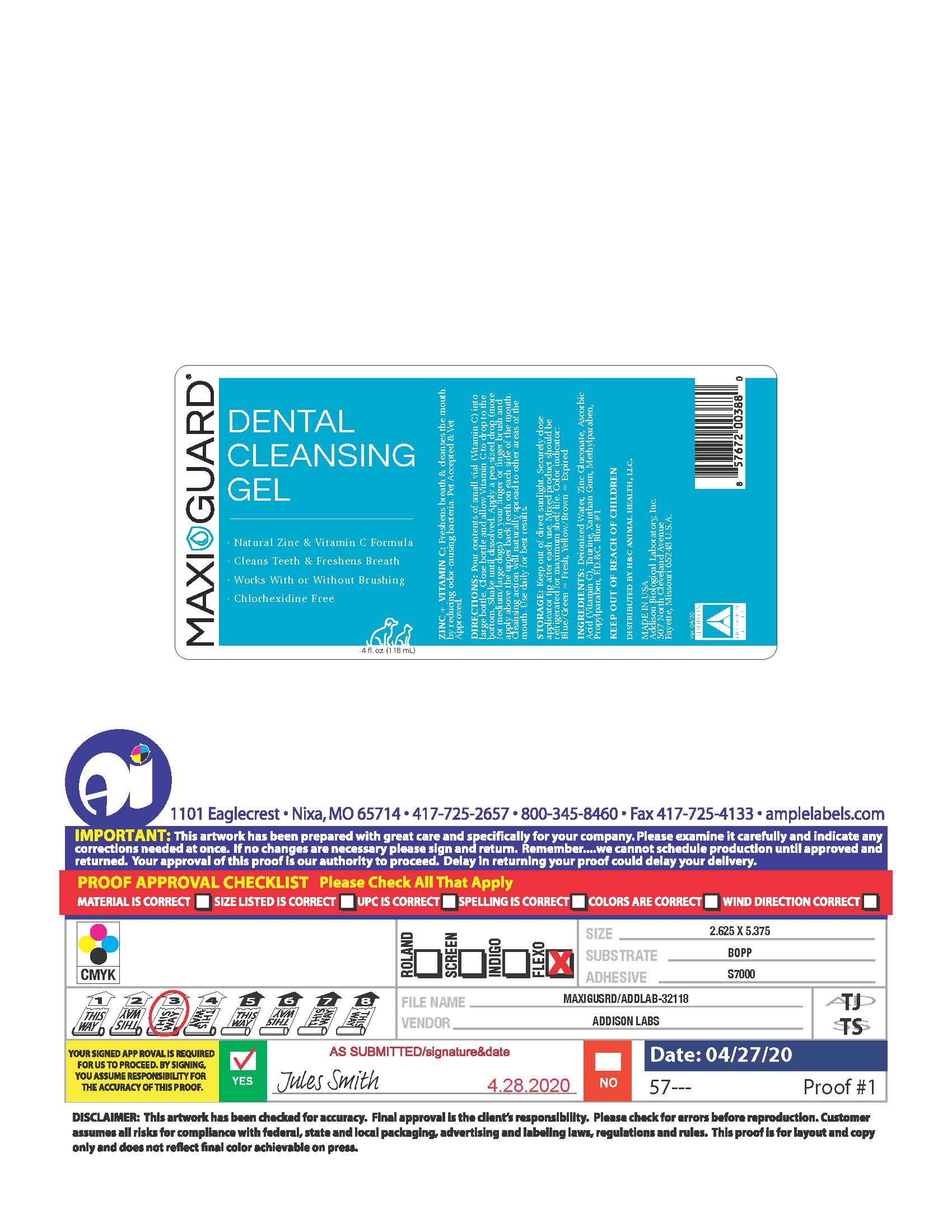 DRUG LABEL: Maxi/Guard Dental Cleansing Gel
NDC: 86137-4159 | Form: GEL
Manufacturer: H & C Animal Health LLC
Category: animal | Type: OTC ANIMAL DRUG LABEL
Date: 20251201

ACTIVE INGREDIENTS: ZINC GLUCONATE 0.022 g/1 mL
INACTIVE INGREDIENTS: WATER; ASCORBIC ACID; TAURINE; XANTHAN GUM; METHYLPARABEN; PROPYLPARABEN; FD&C BLUE NO. 1

Maxi/Guard Dental Cleansing Gel

INDICATIONS AND USAGE

Zinc + Vitamin C: Freshens breath & cleanses the mouth by reducing odor-causing bacteria. Pet Accepted & Vet Approved.

Directions: Pour contents of small vial (Vitamin C) into large bottle. Close bottle and allow Vitamin C to drop to the bottom. Shake until dissolved. Apply a pea -sized (more for medium/large dogs) on your finger or finger brush and apply above the upper back teeth on each side of the mouth. Cleansing action will naturally spread to other areas of the mouth. Use daily for best results.

STORAGE AND HANDLING

STORAGE: Keep out of direct sunlight. Securely close applicator tip after each use. Mixed product should be refridgerated for maximum shelf life.

Color indiator: Blue/Green = Fresh , Yellow or brown = expired.

INACTIVE INGREDIENT

INGREDIENTS: Deionized Water, Zinc Gluconate, Ascorbic Acid (Vitamin C), Taurine, Xanthan Gum, Methylparaben, Propylparaben, F.D.&C. Blue #1

KEEP OUT OF REACH OF CHILDREN

DISTRIBUTED BY H&c ANIMAL HEALTH, LLC.

Made in the U.S.A.

Addison Biological Laboratory, Inc.

507 North Cleveland Avenue
Fayette, Missouri 65248
www.addisonlabs.com

Rev. 04/20

Package label, display panel

MAXI GUARD

DENTAL CLEANSING GEL

- Natural Zinc & Vitamin C Formula
- Cleans Teeth & Freshens Breath
- Works with or Without Brushing
- Chlorhexidine Free

4fl.oz. (118 mL)

Zinc + Vitamin C: Freshens breath & cleanses the mouth by reducing odor-causing bacteria. Pet Accepted & Vet Approved.

Directions: Pour contents of small vial (Vitamin C) into large bottle. Close bottle and allow Vitamin C to drop to the bottom. Shake until dissolved. Apply a pea -sized (more for medium/large dogs) on your finger or finger brush and apply above the upper back teeth on each side of the mouth. Cleansing action will naturally spread to other areas of the mouth. Use daily for best results.

STORAGE: Keep out of direct sunlight. Securely close applicator tip after each use. Mixed product should be refridgerated for maximum shelf life.

Color indiator: Blue/Green = Fresh , Yellow or brown = expired.

INGREDIENTS: Deionized Water, Zinc Gluconate, Ascorbic Acid (Vitamin C), Taurine, Xanthan Gum, Methylparaben, Propylparaben, F.D.&C. Blue #1

KEEP OUT OF REACH OF CHILDREN

DISTRIBUTED BY H&C ANIMAL HEALTH, LLC.

Made in the U.S.A.

Addison Biological Laboratory, Inc.

507 North Cleveland Avenue
Fayette, Missouri 65248
www.addisonlabs.com

Rev. 04/20